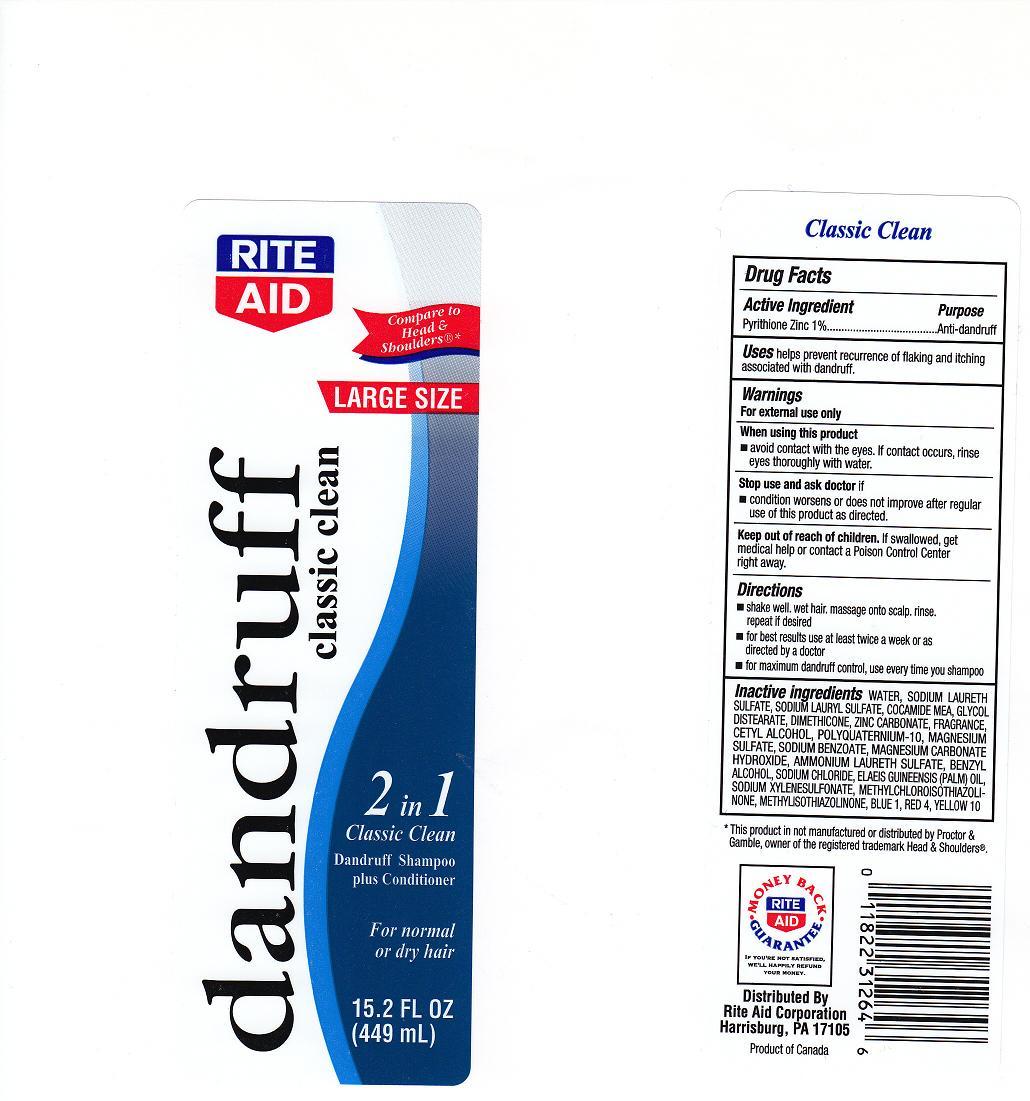 DRUG LABEL: Rite Aid Dandruff
NDC: 11822-4101 | Form: SHAMPOO
Manufacturer: Rite Aid Corporation
Category: otc | Type: HUMAN OTC DRUG LABEL
Date: 20101020

ACTIVE INGREDIENTS: Pyrithione Zinc 1 mL/100 mL
INACTIVE INGREDIENTS: WATER; SODIUM LAURETH SULFATE; SODIUM LAURYL SULFATE; COCO MONOETHANOLAMIDE; GLYCOL DISTEARATE; DIMETHICONE; ZINC CARBONATE; CETYL ALCOHOL; MAGNESIUM SULFATE ANHYDROUS; SODIUM BENZOATE; ALMAGATE; AMMONIUM LAURETH-2 SULFATE; BENZYL ALCOHOL; SODIUM CHLORIDE; PALM OIL; METHYLCHLOROISOTHIAZOLINONE; METHYLISOTHIAZOLINONE; D&C YELLOW NO. 10; FD&C BLUE NO. 1; FD&C RED NO. 4

Drug Facts - Back Label

Active Ingredient

Pyrithione Zinc 1%

Purpose

Anti-dandruff

Uses

Helps prevent recurrence of flaking and itching associated with dandruff

Warnings

For external use only

When using this product

Avoid contact with eyes. If contact occurs, rinse eyes with water thoroughly

Stop use and ask doctor if

Conditions worsens or does not improve after regular use of this product as directed

Keep out of reach of children

If swallowed, get medical help or contact a Poison Control Center right away

Directions

- Shake well, wet hair, massage onto scalp, rinse. Repeat if desired.
- For best results use at least twice a week or as directed by a doctor.
- For maximum dandruff control, use every time you shampoo

Inactive Ingredients

Water, Sodium Laureth Sulfate, Sodium Lauryl Sulfate, Cocamide MEA, Glycol Distearate, Dimethicone, Zinc Carbonate, Fragrance, Cetyl Alcohol, Polyquaternium-10, Magnesium Sulfate, Sodium Benzoate, Magnesium Carbonate Hydroxide, Ammonium Laureth Sulfate, Benzyl Alcohol, Sodium Chloride, Elaeis Guineensis (Palm) Oil, Sodium Xylenesulfonate, Methylchloroisothiazolinone, Methylisothiazolinone, Yellow 10, Blue 1, Red 4

Principle Display Panel

Rite Aid Dandruff classic clean

Large Size

Compare to Head and Shoulder®

2 in 1 Classic Clean

Dandruff Shampoo plus Conditioner

For normal or dry hair

15.2 FL OZ (449 mL)

ra.jpg